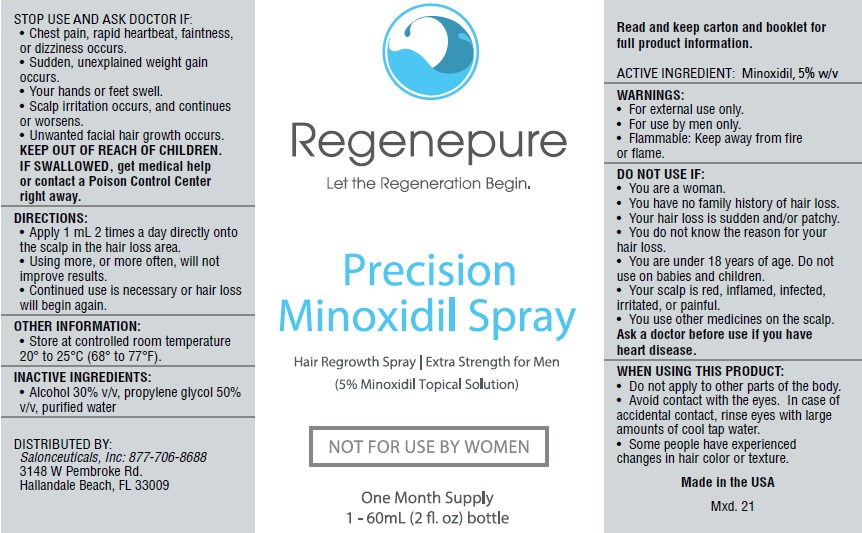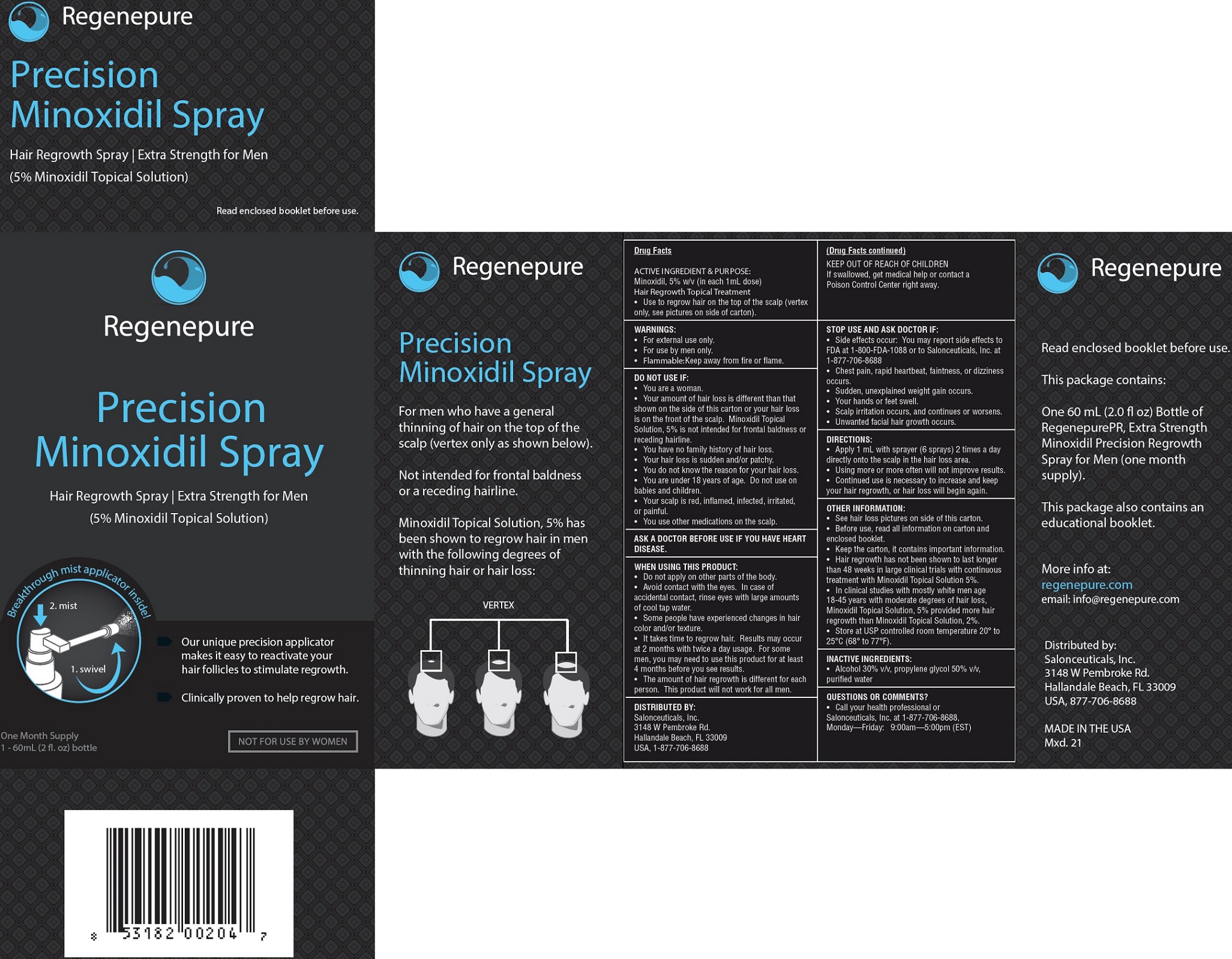 DRUG LABEL: Regenpure Precision
NDC: 71290-813 | Form: LIQUID
Manufacturer: Salonceuticals, Inc.
Category: otc | Type: HUMAN OTC DRUG LABEL
Date: 20170306

ACTIVE INGREDIENTS: MINOXIDIL 50 mg/1 mL
INACTIVE INGREDIENTS: ALCOHOL; PROPYLENE GLYCOL; WATER

Regenpure Precision Minoxidil

ACTIVE INGREDIENT

Minoxidil, 5% w/v (in each 1mL dose)

PURPOSE:

Hair Regrowth Topical Treatment

Use

- to regrow hair on the top of the scalp (vertex only, see pictures on side of carton).

WARNINGS:

• For external use only.
• For use by men only.
• Flammable: Keep away from fire or flame.

DO NOT USE IF:

• You are a woman.

• Your amount of hair loss is different than that shown on the side of this carton or your hair loss is on the front of the scalp. Minoxidil Topical Solution, 5% is not intended for frontal baldness or receding hairline.
• You have no family history of hair loss.
• Your hair loss is sudden and/or patchy.
• You do not know the reason for your hair loss.
• You are under 18 years of age. Do not use on babies and children.
• Your scalp is red, inflamed, infected, irritated, or painful.
• You use other medications on the scalp.

ASK A DOCTOR BEFORE USE IF

YOU HAVE HEART DISEASE.

WHEN USING THIS PRODUCT:

• Do not apply on other parts of the body.
• Avoid contact with the eyes. In case of accidental contact, rinse eyes with large amounts of cool tap water.
• Some people have experienced changes in hair color and/or texture.
• It takes time to regrow hair. Results may occur at 2 months with twice a day usage. For some men, you may need to use this product for at least
4 months before you see results.
• The amount of hair regrowth is different for each person. This product will not work for all men.

KEEP OUT OF REACH OF CHILDREN

If swallowed, get medical help or contact a Poison Control Center right away.

STOP USE AND ASK DOCTOR IF:

• Side effects occur: You may report side effects to FDA at 1-800-FDA-1088 or to Salonceuticals, Inc. at 1-877-706-8688
• Chest pain, rapid heartbeat, faintness, or dizziness occurs.
• Sudden, unexplained weight gain occurs.
• Your hands or feet swell.
• Scalp irritation occurs, and continues or worsens.
• Unwanted facial hair growth occurs.

DIRECTIONS:

• Apply 1 mL with sprayer (6 sprays) 2 times a day directly onto the scalp in the hair loss area.
• Using more or more often will not improve results.
• Continued use is necessary to increase and keep your hair regrowth, or hair loss will begin again.

OTHER INFORMATION:

• See hair loss pictures on side of this carton.
• Before use, read all information on carton and enclosed booklet.
• Keep the carton, it contains important information.
• Hair regrowth has not been shown to last longer than 48 weeks in large clinical trials with continuous treatment with Minoxidil Topical Solution 5%.
• In clinical studies with mostly white men age 18-45 years with moderate degrees of hair loss, Minoxidil Topical Solution, 5% provided more hair regrowth than Minoxidil Topical Solution, 2%.
• Store at USP controlled room temperature 20° to 25°C (68° to 77°F).

INACTIVE INGREDIENTS:

• Alcohol 30% v/v, propylene glycol 50% v/v, purified water

QUESTIONS OR COMMENTS?

• Call your health professional or Salonceuticals, Inc. at 1-877-706-8688, Monday—Friday: 9:00am—5:00pm (EST)